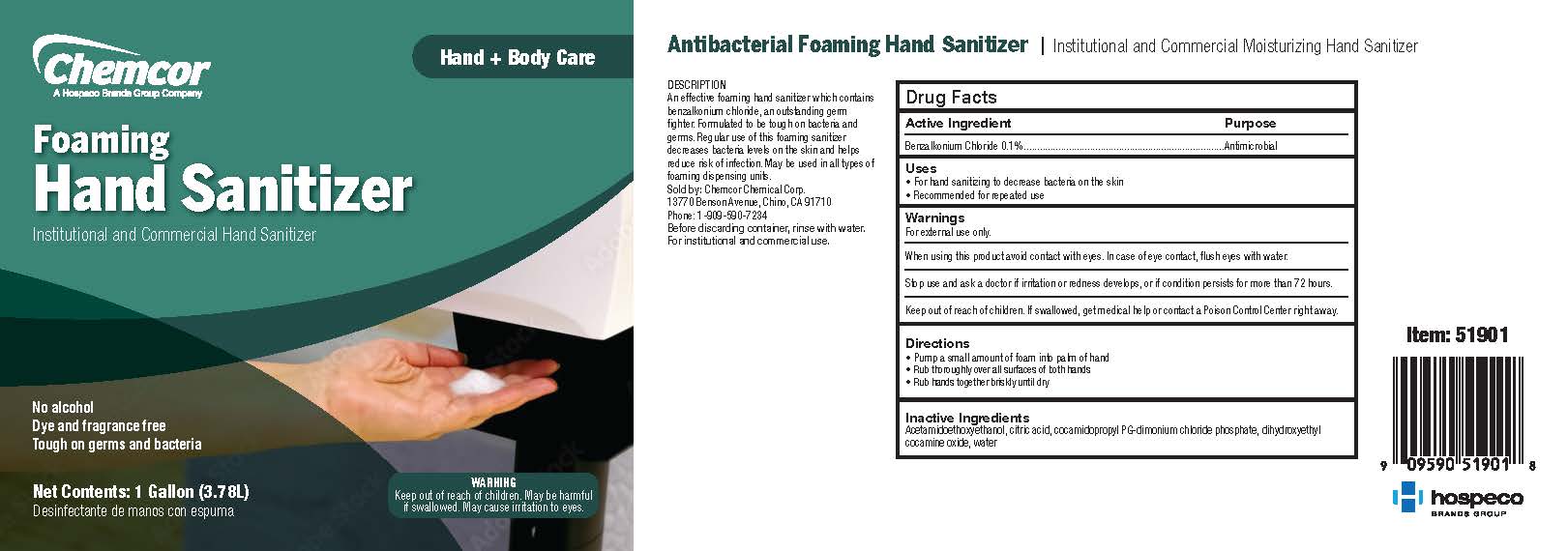 DRUG LABEL: Chemcor Chemical Foaming Hand Sanitizer
NDC: 68041-519 | Form: LIQUID
Manufacturer: Chemcor Chemical Corporation
Category: otc | Type: HUMAN OTC DRUG LABEL
Date: 20251222

ACTIVE INGREDIENTS: BENZALKONIUM CHLORIDE 0.0013 mg/1 mL
INACTIVE INGREDIENTS: WATER; COCAMIDOPROPYL PG-DIMONIUM CHLORIDE PHOSPHATE; DIHYDROXYETHYL COCAMINE OXIDE; ACETAMIDOETHOXYETHANOL; CITRIC ACID MONOHYDRATE

Foaming Hand Sanitizer

Active Ingredient

Benzalkonium Chloride 0.1%

Purpose

Antimicrobial

Uses

- For hand sanitizing to decrease bacteria on the skin
- Recommended for repeated use

Warnings

For external use only

When using this product avoid contact with eyes. In case of eye contact, flush eyes with water.

Stop use and ask a doctor if irritation or redness develops, or if condition persists for more than 72 hours.

Keep out of reach of children. If swallowed, get medical help or contact a Poison Control Center right away.

Directions

- Pump a small amount of foam into palm of hand
- Rub thoroughly over all surfaces of both hands
- Rub hands together briskly until dry

Inactive Ingredients

Water, Cocamidopropyl PG-dimonium Chloride Phosphate, Dihydroxyethyl cocamine oxide, acetamidoethoxyethanol, citric acid.

no alcohol

dye and fragrance free

tough on germs and bacteria

CHEMCOR

CHEMICAL CORP

CHINO, CA 91710

CHEMCORCHEMICAL.COM

WARNING

KEEP OUT OF REACH OF CHILDREN.

MAY BE HARMFUL IF SWALLOWED.

MAY CAUSE EYE IRRITATION.

SEE BACK PANEL FOR ADDITIONAL PRECAUTIONS AND FIRST AID.

institutional & commercial hand Sanitizer

Before discarding container, rinse with water.

For institutional and commercial use.